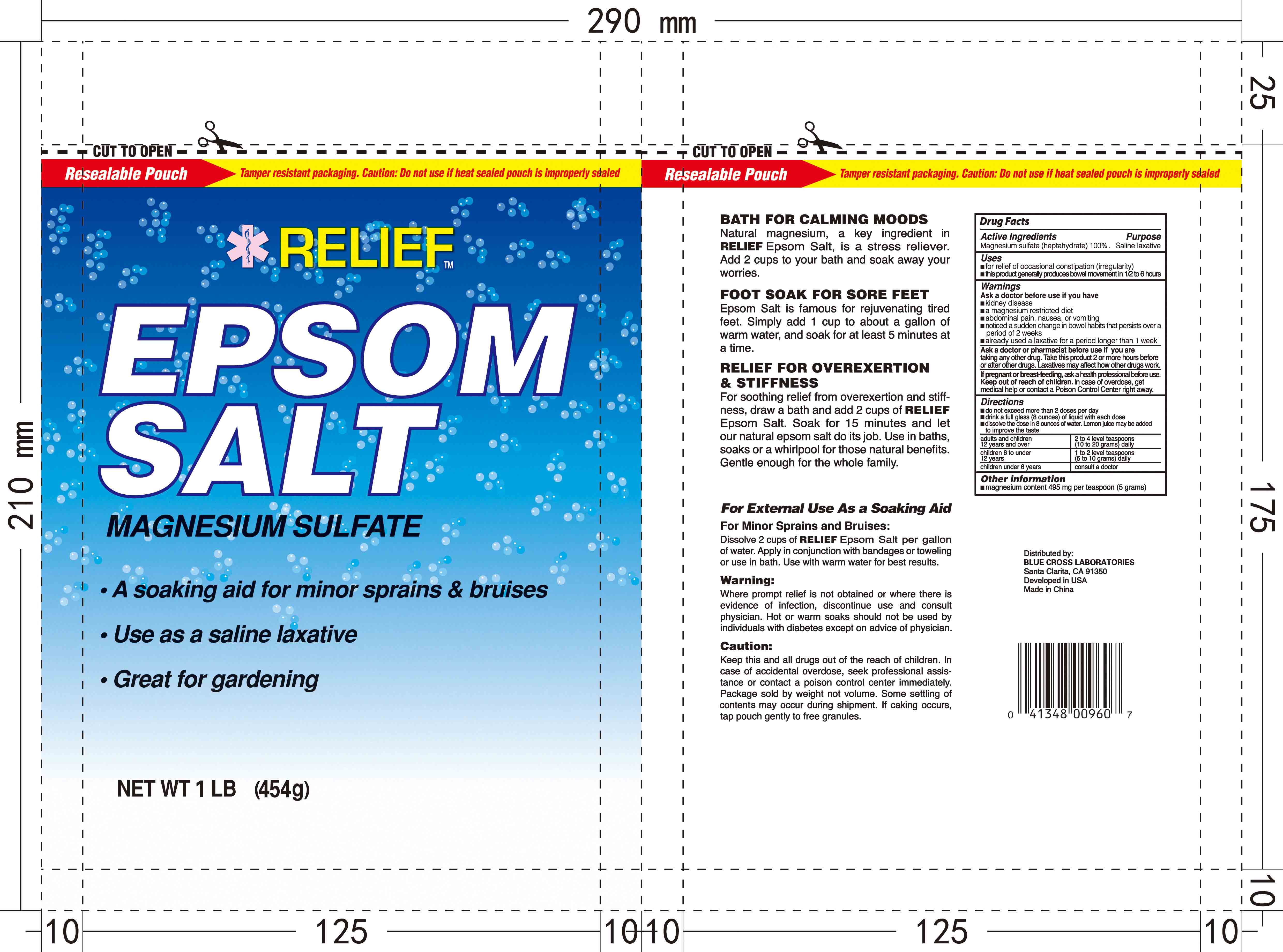 DRUG LABEL: Epsom Salts
NDC: 22431-124 | Form: GRANULE
Manufacturer: Blue Cross Laboratories, Inc.
Category: otc | Type: HUMAN OTC DRUG LABEL
Date: 20221115

ACTIVE INGREDIENTS: MAGNESIUM SULFATE HEPTAHYDRATE 100 g/100 g

Relief Epsom Salt

Active Ingredients Purpose
Magnesium Sulfate [heptahydrate]100% Saline Laxative

PURPOSE

-For relief of occasional constipation (irregularity)

-this product generally produces bowel movement in 1/2 to 6 hours

Keep out of reach of children

INDICATIONS AND USAGE

-For relief of occasional constipation (irregularity)

-this product generally produces bowel movement in 1/2 to 6 hours

Warnings

Ask a doctor is you have

- kidney disease

- a magnesium restricted diet

- abdominal pain, nausea, or vomiting

- noticed a sudden change in bowel habits that persists over a period of 2 weeks

- already used a laxative for a period longer than 1 week

Ask a doctor of pharmacist before use if you are taking any other drug. Take this product 2 or more hours before or after other drugs. Laxatives may affect how other drugs work.

If pregnant or breast-feeding, as a health professional before use. Keep out of reach of children. In case of overdose, get medical help or contact a Poison Control Center right away.

Directions

-do not exceed more than 2 doses per day

-drink a full glass (8 ounces) of liquid with each dose

-dissolve the dose in 8 ounces of water. Lemon juice may be added to improve the taste.

-adults and children 12 years and over: 2 to 4 level teaspoons (10 to 20 grams) daily

-children 6 to under 12 years: 1 to 2 level teaspoons (5 to 10 grams) daily

-children under 6 years: consult a doctor

Other information

Magnesium content: 495 mg per teaspoon

PACKAGE LABEL

Relief

Epsom Salt

Magnesium Sulfate

A Soaking aid for minor sprains & bruises

Use as a saline laxative

NET WT 16 Oz (1 LB) 454 g